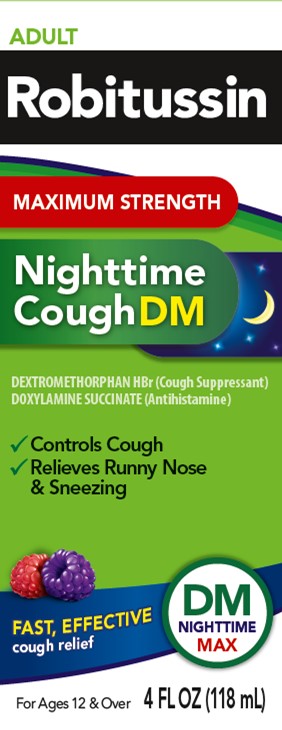 DRUG LABEL: Robitussin Maximum Strength Nighttime Cough DM
NDC: 0031-8718 | Form: SOLUTION
Manufacturer: Haleon US Holdings LLC
Category: otc | Type: HUMAN OTC DRUG LABEL
Date: 20251030

ACTIVE INGREDIENTS: DEXTROMETHORPHAN HYDROBROMIDE 30 mg/20 mL; DOXYLAMINE SUCCINATE 12.5 mg/20 mL
INACTIVE INGREDIENTS: ANHYDROUS CITRIC ACID; CARBOXYMETHYLCELLULOSE SODIUM, UNSPECIFIED; FD&C BLUE NO. 1; FD&C RED NO. 40; GLYCERIN; DEXTROSE, UNSPECIFIED FORM; MENTHOL, UNSPECIFIED FORM; POLYETHYLENE GLYCOL, UNSPECIFIED; PROPYLENE GLYCOL; WATER; SODIUM BENZOATE; SODIUM CITRATE, UNSPECIFIED FORM; SUCRALOSE; TRIACETIN; XANTHAN GUM

Drug Facts

Active ingredients (in each 20 mL)

Dextromethorphan HBr, USP 30 mg

Doxylamine Succinate, USP 12.5 mg

Purposes

Cough suppressant

Antihistamine

Uses

- temporarily relieves cough due to minor throat and bronchial irritation as may occur with a cold
- temporarily relieves these symptoms due to hay fever or other upper respiratory allergies:
  - runny nose
  - sneezing
  - itchy, watery eyes
  - itching of the nose or throat
- controls the impulse to cough to help you sleep

Warnings

Do not use

- to sedate a child or to make a child sleepy
- if you are now taking a prescription monoamine oxidase inhibitor (MAOI) (certain drugs for depression, psychiatric, or emotional conditions, or Parkinson's disease), or for 2 weeks after stopping the MAOI drug. If you do not know if your prescription drug contains an MAOI, ask a doctor or pharmacist before taking this product.

Ask a doctor before use if you have

- trouble urinating due to an enlarged prostate gland
- glaucoma
- a cough that occurs with too much phlegm (mucus)
- a breathing problem or chronic cough that lasts or as occurs with smoking, asthma, chronic bronchitis or emphysema

Ask a doctor or pharmacist before use if you aretaking sedatives or tranquilizers

When using this product

- do not use more than directed
- marked drowsiness may occur
- avoid alcoholic drinks
- alcohol, sedatives, and tranquilizers may increase drowsiness
- be careful when driving a motor vehicle or operating machinery
- excitability may occur, especially in children

Stop use and ask a doctor ifcough lasts more than 7 days, comes back, or is accompanied by fever, rash, or persistent headache. These could be signs of a serious condition.

PREGNANCY OR BREAST FEEDING

If pregnant or breast-feeding,ask a health professional before use.

Keep out of reach of children.In case of overdose, get medical help or contact a Poison Control Center right away.

Directions

- measure only with dosing cup provided
- keep dosing cup with product
- mL = milliliter
- do not take more than 4 doses in any 24-hour period
- this adult product is not intended for use in children under 12 years of age

age | dose
adults and children 12 years and over | 20 mL every 6 hours
children under 12 years | do not use

Other information

- each 20 mL contains:sodium 14 mg
- store at 20-25°C (68-77°F)

Inactive ingredients

anhydrous citric acid, carboxymethylcellulose sodium, FD&C blue no. 1, FD&C red no. 40, glycerin, liquid glucose, menthol, natural and artificial flavors, polyethylene glycol, propylene glycol, purified water, sodium benzoate, sodium citrate, sucralose, triacetin, xanthan gum

Questions or comments?

call weekdays from 9 AM to 5 PM EST at 1-800-245-1040

Additional Information

Do Not Use if foil seal is missing or broken.

PARENTS:

Learn about teen medicine abuse

www.StopMedicineAbuse.org

PRINCIPAL DISPLAY PANEL

ADULT

Robitussin

MAXIMUM STRENGTH

Nighttime
Cough DM

DEXTROMETHORPHAN HBr (Cough Suppressant)
DOXYLAMINE SUCCINATE (Antihistamine)

- Controls Cough
- Relieves Runny Nose& Sneezing

FAST, EFFECTIVE
cough relief

DM
NIGHTTIME
MAX

For Ages 12 & Over
4 FL OZ (118 mL)